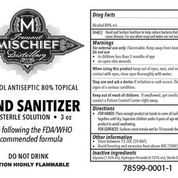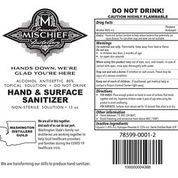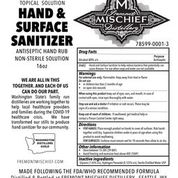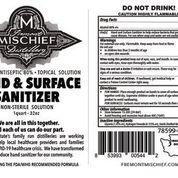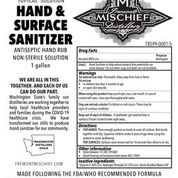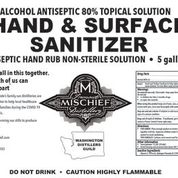 DRUG LABEL: Fremont Mischief Hand Sanitizer
NDC: 78599-0001 | Form: LIQUID
Manufacturer: Fremont Mischief Inc
Category: otc | Type: HUMAN OTC DRUG LABEL
Date: 20200602

ACTIVE INGREDIENTS: ALCOHOL 141.6 mL/177 mL
INACTIVE INGREDIENTS: GLYCERIN 2.57 mL/177 mL; HYDROGEN PEROXIDE 0.23 mL/177 mL; WATER 32.6 mL/177 mL

78599-0001-1 78599-0001-2 78599-0001-3 78599-0001-4 78599-0001-5 78599-0001-6

Active Ingredient(s)

Alcohol 80% v/v. Purpose: Antiseptic

Purpose

Antiseptic, Hand Sanitizer

Use

Hand Sanitizer to help reduce bacteria that potentially can cause disease. For use when soap and water are not available.

Warnings

For external use only. Flammable. Keep away from heat or flame

Do not use

- in children less than 2 months of age
- on open skin wounds

When using this product keep out of eyes, ears, and mouth. In case of contact with eyes, rinse eyes thoroughly with water.
Stop use and ask a doctor if irritation or rash occurs. These may be signs of a serious condition.
Keep out of reach of children. If swallowed, get medical help or contact a Poison Control Center right away.

Stop use and ask a doctor if irritation or rash occurs. These may be signs of a serious condition.

Keep out of reach of children. If swallowed, get medical help or contact a Poison Control Center right away.

Directions

- Place enough product on hands to cover all surfaces. Rub hands together until dry.
- Supervise children under 6 years of age when using this product to avoid swallowing.

Other information

- Store between 15-30C (59-86F)
- Avoid freezing and excessive heat above 40C (104F)

Inactive ingredients

glycerin, hydrogen peroxide, purified water USP

Package Label - Principal Display Panel

88.72 mL NDC: 78599-0001-1

384.46 mL NDC: 78599-0001-2

473.18 mL NDC: 78599-0001-3

946.35 mL NDC: 78599-0001-4

3785.4 mL NDC: 78599-0001-5

18927 mL NDC: 78599-0001-6